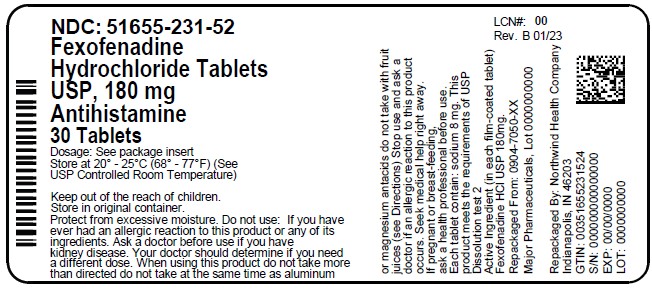 DRUG LABEL: Fexofenadine Hydrochloride
NDC: 51655-231 | Form: TABLET
Manufacturer: Northwind Health Company, LLC
Category: otc | Type: HUMAN OTC DRUG LABEL
Date: 20260101

ACTIVE INGREDIENTS: FEXOFENADINE HYDROCHLORIDE 180 mg/1 1
INACTIVE INGREDIENTS: SILICON DIOXIDE; CROSCARMELLOSE SODIUM; HYPROMELLOSES; FERRIC OXIDE RED; FERRIC OXIDE YELLOW; ANHYDROUS LACTOSE; STARCH, CORN; POLYETHYLENE GLYCOL, UNSPECIFIED; LACTOSE MONOHYDRATE; STEARIC ACID; TITANIUM DIOXIDE

Active ingredient (in each film-coated tablet)

Fexofenadine HCL 180 mg

Purpose

Antihistamine

Uses

temporarily relieves these symptoms due to hay fever or other upper respiratory allergies:

- runny nose
- itchy, watery eyes
- sneezing
- itching of the nose or throat

Warnings

Do not use

if you have ever had an allergic reaction to this product or any of its ingredients.

Ask a doctor before use if you have

kidney disease. Your doctor should determine if you need a different dose.

When using this product

- do not take more than directed
- do not take at the same time as aluminum or magnesium antacids
- do not take with fruit juices (see Directions)

Stop use and ask a doctor if

an allergic reaction to this product occurs. Seek medical help right away.

If pregnant or breast-feeding,

ask a health professional before use.

Keep out of reach of children.

In case of overdose, get medical help or contact a Poison Control Center right away (1-800-222-1222).

Directions

adults and children 12 years of age and over | take one 180 mg tablet with water once a day; do not take more than 1 tablet in 24 hours
children under 12 years of age | do not use
adults 65 years of age and older | ask a doctor
consumers with kidney disease | ask a doctor

Other information

- each tablet contain: sodium 8 mg
- store between 20 to 25°C (68 to 77°F)
- protect from excessive moisture
- this product meets the requirements of USP Dissolution Test 2

Inactive ingredients

anhydrous lactose, colloidal silicon dioxide, corn starch, croscarmellose sodium, hypromellose, lactose monohydrate, polyethylene glycol, pregelatinized starch (maize), red iron oxide, stearic acid, titanium dioxide, and yellow iron oxide

Questions or comments?

Call: 1-800-616-2471

Principal Display Panel

COMPARE TO the active ingredient in ALLEGRA® ALLERGY 24 HOUR*

FEXOFENADINE HYDROCHLORIDE USP 180 mg

Antihistamine

ALLERGY RELIEF

24-HOUR Relief of:

- sneezing
- Runny nose
- Itchy, watery eyes
- Itchy nose or throat

Indoor and Outdoor

Allergy Relief

Non-Drowsy

Capsule Shaped Tablets

*This product is not manufactured or distributed by Chattem Inc., distributor of Allegra® Allergy 24 hour

TAMPER EVIDENT: DO NOT USE IF PRINTED SAFETY SEAL UNDER CAP IS BROKEN OR MISSING

Distributed by:

MAJOR® PHARMACEUTICALS

17177 N Laurel Park Drive, Suite 233

Livonia, MI 48152

Principal Display Panel

NDC: 51655-231-52